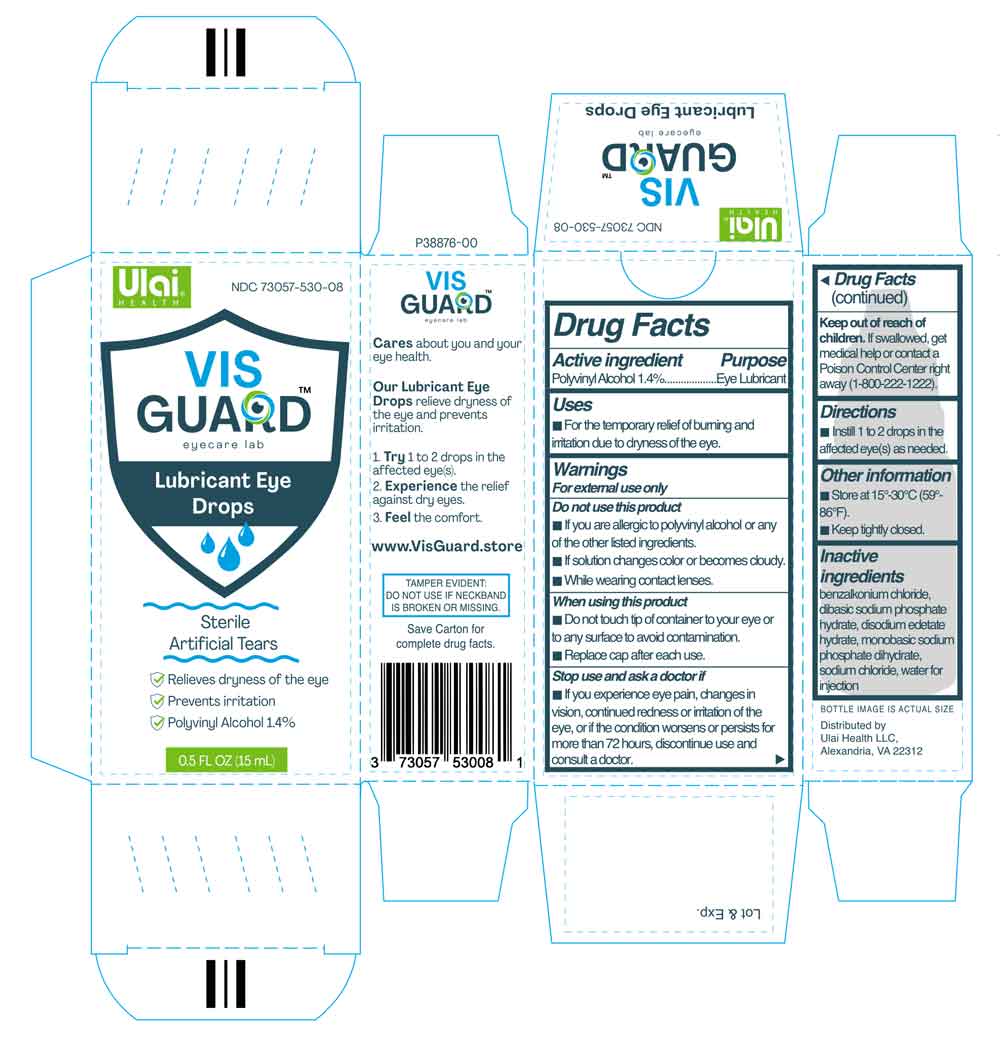 DRUG LABEL: Vis Guard Lubricant Eye Drops
NDC: 73057-530 | Form: SOLUTION/ DROPS
Manufacturer: Ulai Health LLC
Category: otc | Type: HUMAN OTC DRUG LABEL
Date: 20260113

ACTIVE INGREDIENTS: POLYVINYL ALCOHOL, UNSPECIFIED 1.4 mg/100 mL
INACTIVE INGREDIENTS: BENZALKONIUM CHLORIDE; SODIUM CHLORIDE; EDETATE DISODIUM; SODIUM PHOSPHATE, MONOBASIC, DIHYDRATE; SODIUM PHOSPHATE, DIBASIC, DODECAHYDRATE; WATER

Active ingredient

Polyvinyl alcohol 1.4%

Purpose

Lubricant

Uses

For the temporary relief of burning and irritation due to dryness of the eye.

Warnings

For external use only

Do not use this product

If you are allergic to polyvinyl alcohol or any of the other listed ingredients.
If solution changes color or becomes cloudy.
While wearing contact lenses.

When using this product

Do not touch tip of container to your eye or to any surface to avoid contamination.
Replace cap after each use.

Stop use and ask a doctor if

If you experience eye pain, changes in vision, continued redness or irritation of the eye, or if the condition worsens or persists for more than 72 hours, discontinue use and consult a doctor.

Keep out of reach of children.

If swallowed, get medical help or contact a Poison Control Center right away (1-800-222-1222).

Directions

Instill 1 to 2 drops in the affected eye(s) as needed.

Other information

Store at 15°-30°C (59°-86°F).
Keep tightly closed.

Inactive ingredients

benzalkonium chloride, dibasic sodium phosphate hydrate, disodium edetate hydrate, monobasic sodium phosphate dihydrate, sodium chloride, water for injection